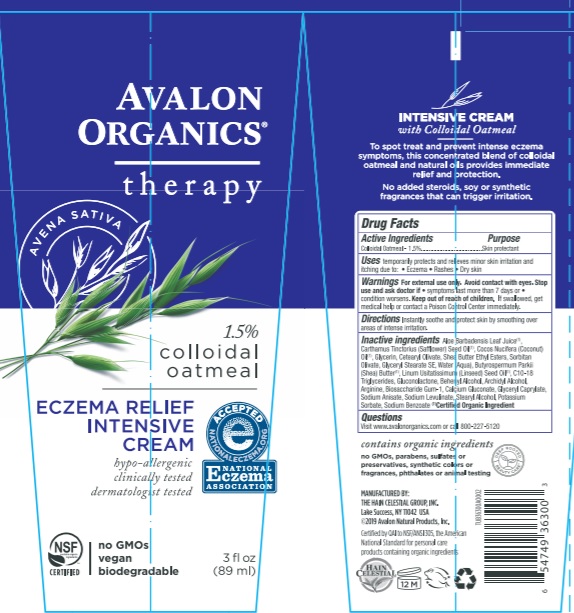 DRUG LABEL: AV3630000 Avalon Organics Eczema Relief Intensive
NDC: 61995-1300 | Form: CREAM
Manufacturer: The Hain Celestial Group, Inc.
Category: otc | Type: HUMAN OTC DRUG LABEL
Date: 20210412

ACTIVE INGREDIENTS: OATMEAL 1.5 g/100 g
INACTIVE INGREDIENTS: SAFFLOWER OIL; SHEA BUTTER; CETEARYL OLIVATE; ARGININE; CALCIUM GLUCONATE; COCONUT OIL; ALOE VERA LEAF; GLYCERIN; WATER; GLYCERYL STEARATE SE; SODIUM BENZOATE; GLUCONOLACTONE; LINSEED OIL; STEARYL ALCOHOL; DOCOSANOL; POTASSIUM SORBATE; SORBITAN OLIVATE; SODIUM LEVULINATE; GLYCERYL CAPRYLATE; C10-18 TRIGLYCERIDES; SODIUM ANISATE; SHEA BUTTER ETHYL ESTERS

AV3630000 Avalon Organics Eczema Relief Intensive

Active Ingredient

Colloidal Oatmeal - 1.5%

DOSAGE AND ADMINISTRATION

Instantly sootheand protect skin by smoothing over areas of intense irritation.

PURPOSE

Skin Protectant

WARNINGS

For external use only. Avoid contacts with eyes. Stop use and ask a doctor if symptoms last more than 7 days or condition worsens.

Keep out of reach of children. If swallowed get medical help or contact Poison Center immediately.

INACTIVE INGREDIENT

Aloe Barbadensis Leaf Juice (1)

Carthamus Tinctorius (Safflower) Seed Oil (1)

Cocos Nucifera (Coconut) Oil (1)

Glycerin

Cetearyl Olivate

Shea Butter Ethyl Esters

Sorbitan Olivate

Glyceryl Stearate SE

Aqua (Purified Water)

Butyrospermum Parkii (Shea) Butter (1)

Linum Usitatissimum (Linseed) Seed Oil (1)

C10-18 Triglycerides

Gluconolactone

Behenyl Alcohol

Archidyl Alcohol

Arginine

Biosaccharide gum-1

Calcium Gluconate

Glyceryl Caprylate

Sodium Anisate

Sodium Levulinate

Stearyl Alcohol

Potassium Sorbate

Sodium Benzoate

(1) Certified Organic Ingredient

INDICATIONS AND USAGE

Helps protect and relieve skin irritation and itching due to: Eczema, Rashes, Dry skin.